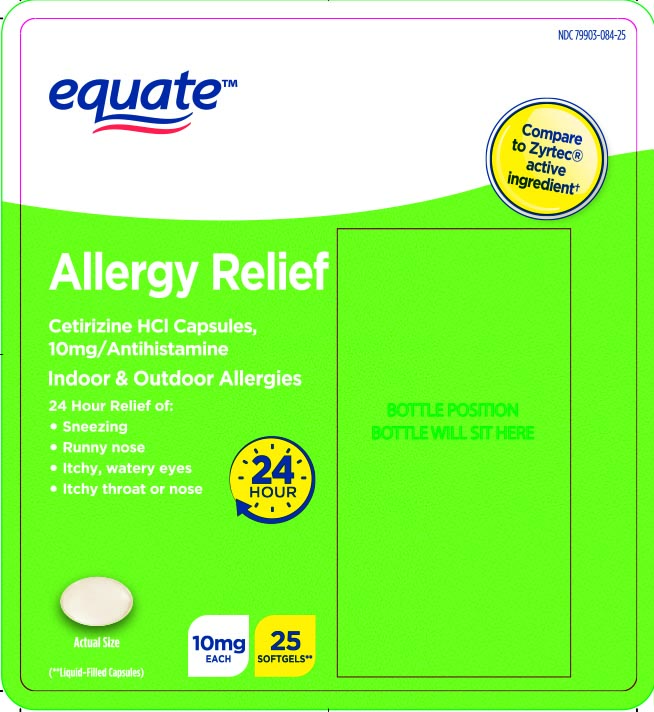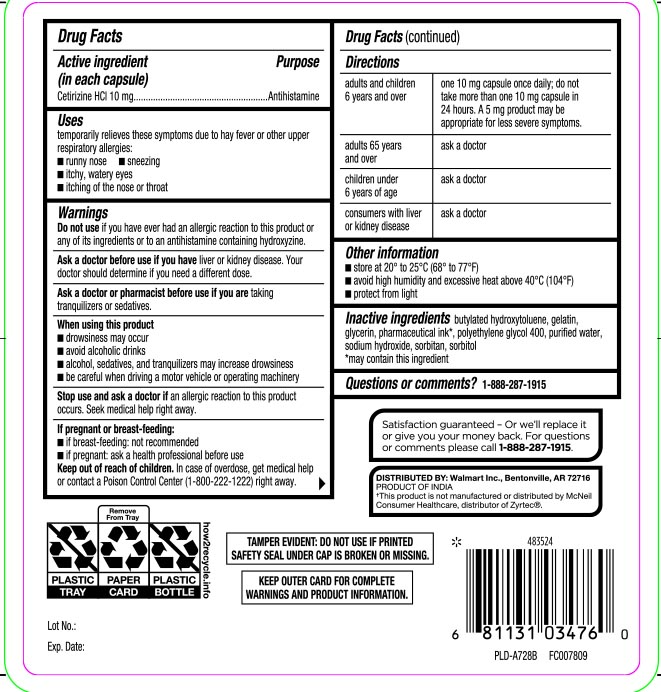 DRUG LABEL: All Day Allergy
NDC: 79903-084 | Form: CAPSULE
Manufacturer: WALMART INC. (see also Equate)
Category: otc | Type: HUMAN OTC DRUG LABEL
Date: 20260220

ACTIVE INGREDIENTS: CETIRIZINE HYDROCHLORIDE 10 mg/1 1
INACTIVE INGREDIENTS: GELATIN; GLYCERIN; MANNITOL; POLYETHYLENE GLYCOL 400; WATER; SODIUM HYDROXIDE; SORBITAN; SORBITOL; BUTYLATED HYDROXYTOLUENE

Cetirizine Hydrochloride Tablets

Active Ingredient (in each capsule)

Cetirizine HCl 10 mg

Purpose

Antihistamine

Uses

temporarily relieves these symptoms due to hay fever or other upper respiratory allergies:

- runny nose
- sneezing
- itchy, watery eyes
- itching of the nose or throat

Do not use

if you have ever had an allergic reaction to this product or any of its ingredients or to an antihistamine containing hydroxyzine.

Ask a doctor before use if you have

liver or kidney disease. Your doctor should determine if you need a different dose.

Ask a doctor or pharmacist before use if you are

taking tranquilizers or sedatives.

When using this product

- drowsiness may occur
- alcohol, sedatives, and tranquilizers may increase drowsiness
- avoid alcoholic drinks
- be careful when driving a motor vehicle or operating machinery

Stop use and ask a doctor if

an allergic reaction to this product occurs. Seek medical help right away.

If pregnant or breast-feeding

- if breast-feeding: not recommended
- if pregnant: ask a health professional before use.

Keep out of reach of children

In case of overdose, get medical help or contact a Poison Control Center (1-800-222-1222) right away.

Directions

Adults and children 6 years and over | One 10 mg capsule once daily; do not take more than one 10 mg capsule in 24 hours. A 5 mg product may be appropriate for less severe symptoms.
Adults 65 years and over | ask a doctor.
Children under 6 years of age | ask a doctor
Consumers with liver or kidney disease | ask a doctor

Other Information

- store at 20o- 25o C (68o to 77o F)
- avoid high humidity and excessive heat above 40o C (104o F)
- protect from light
- swallow whole; do not crush, chew, or dissolve

Inactive Ingredients

Butylated hydroxytolene, gelatin, glycerin, mannitol, pharmaceutical ink, polyethylene glycol 400, purified water, sodium hydroxide, Sorbitan, Sorbitol

Questions or comments?

Call 1-877-753-3935 Monday-Friday 9AM-5PM EST

Principal Display Panel

ORIGINAL PRESCRIPTION STRENGTH

24 Hour Allergy

Cetirizine HCI Capsules 10 mg

Antihistamine

Compare to Zyrtec® active ingredient≠≠

Relieves symptoms associated with allergies

- 24 hour relief of runny nose, sneezing, itchy throat or nose & itchy watery eyes

SOFTGELS

(**Liquid-Filled Capsules)

INDOOR & OUTDOOR ALLERGIES

*This product is not manufactured or distributed by McNeil Consumer Healthcare, distributor of Zyrtec®.

TAMPER EVIDENT: DO NOT USE IF PRINTED SAFETY SEAL UNDER CAP IS BROKEN OR MISSING.

KEEP OUTER CARD FOR COMPLETE WARNINGS AND PRODUCT INFORMATION.

DISTRIBUTED BY: WALGREEN CO.

200 WILMOT RD., DEERFIELD, IL 60015

walgreens.com ©2018 Walgreen Co.

Product Label

Equate Allergy Relief front panel
Equate Allergy Relief Drug Facts Panel